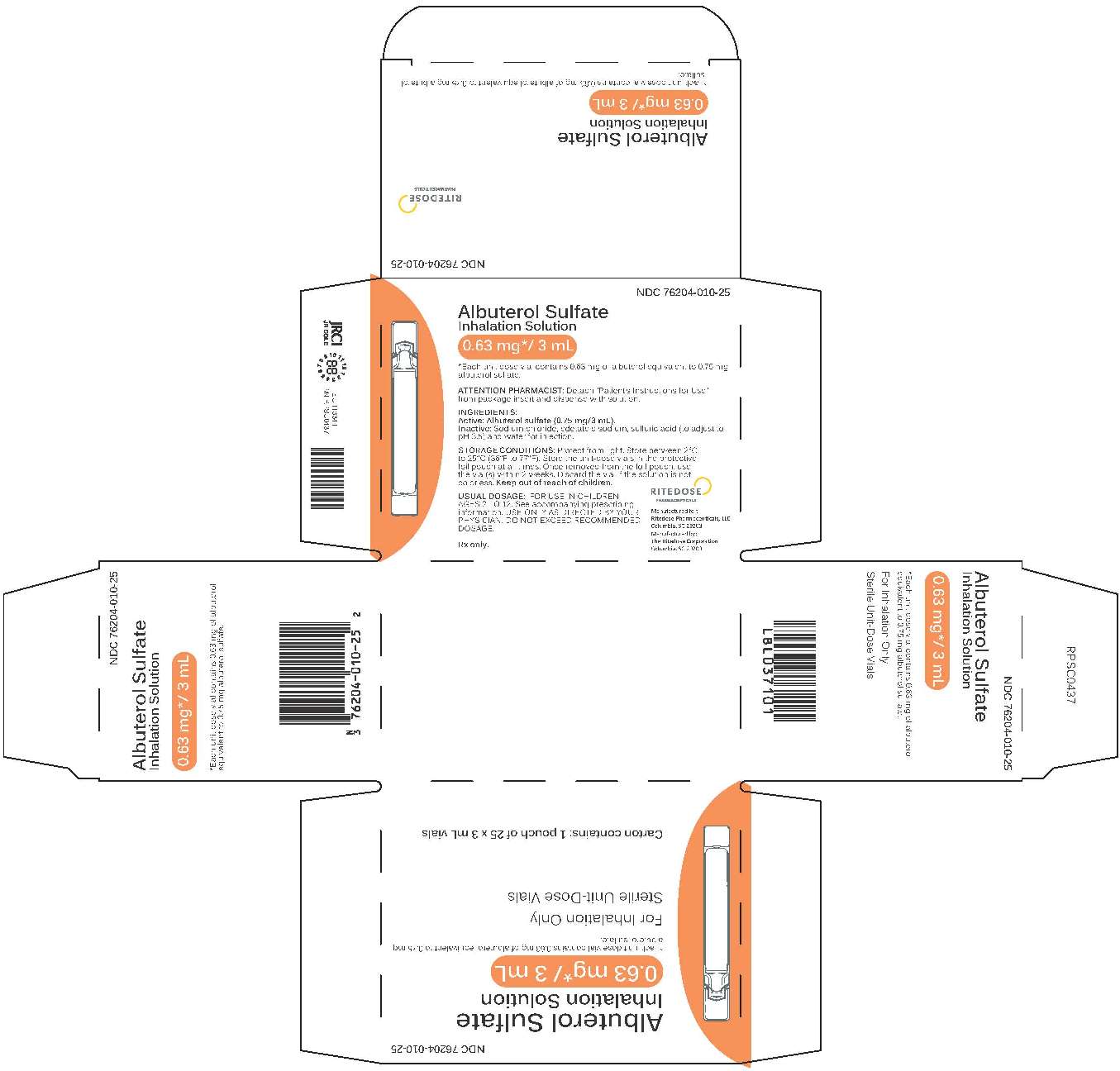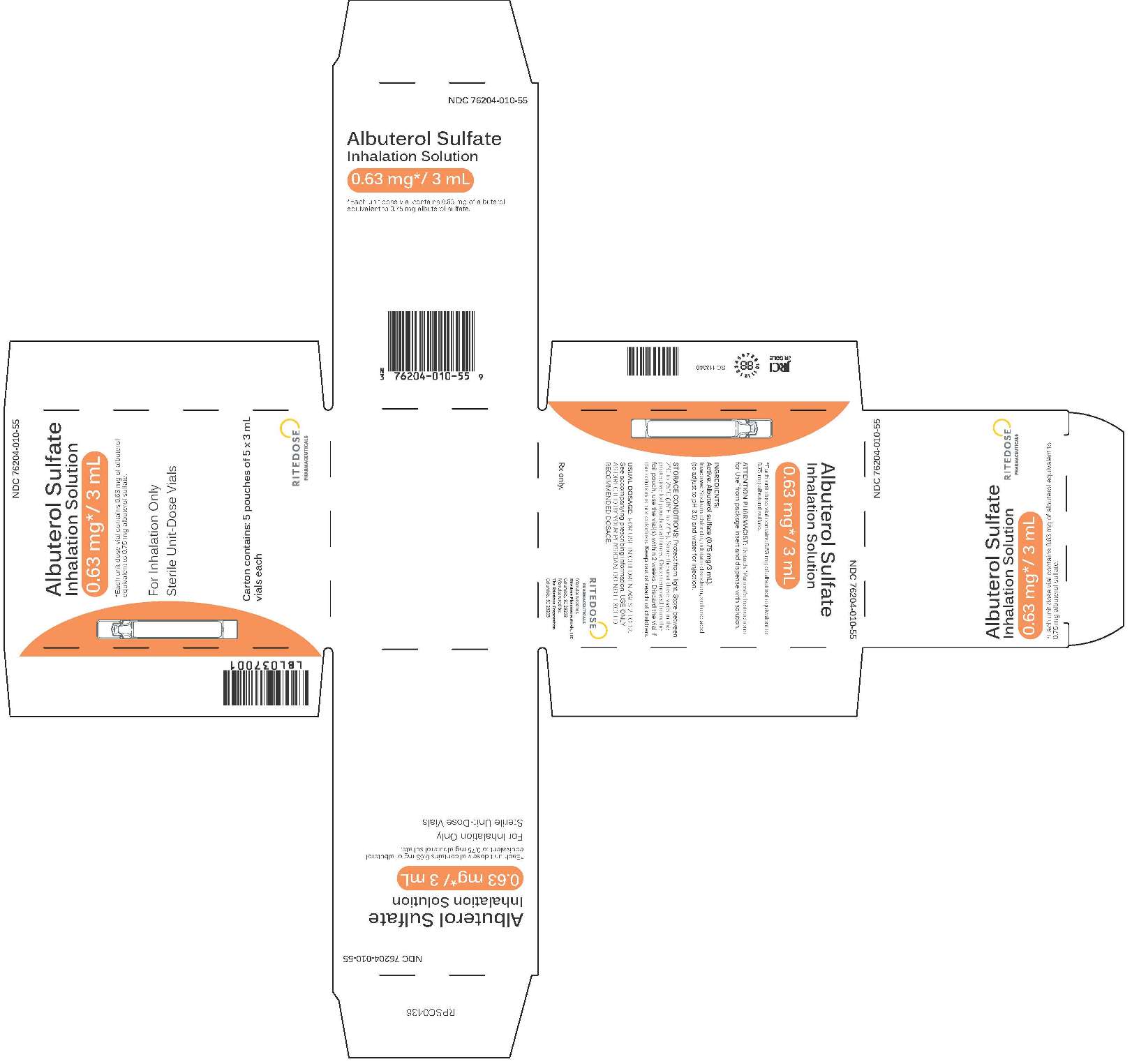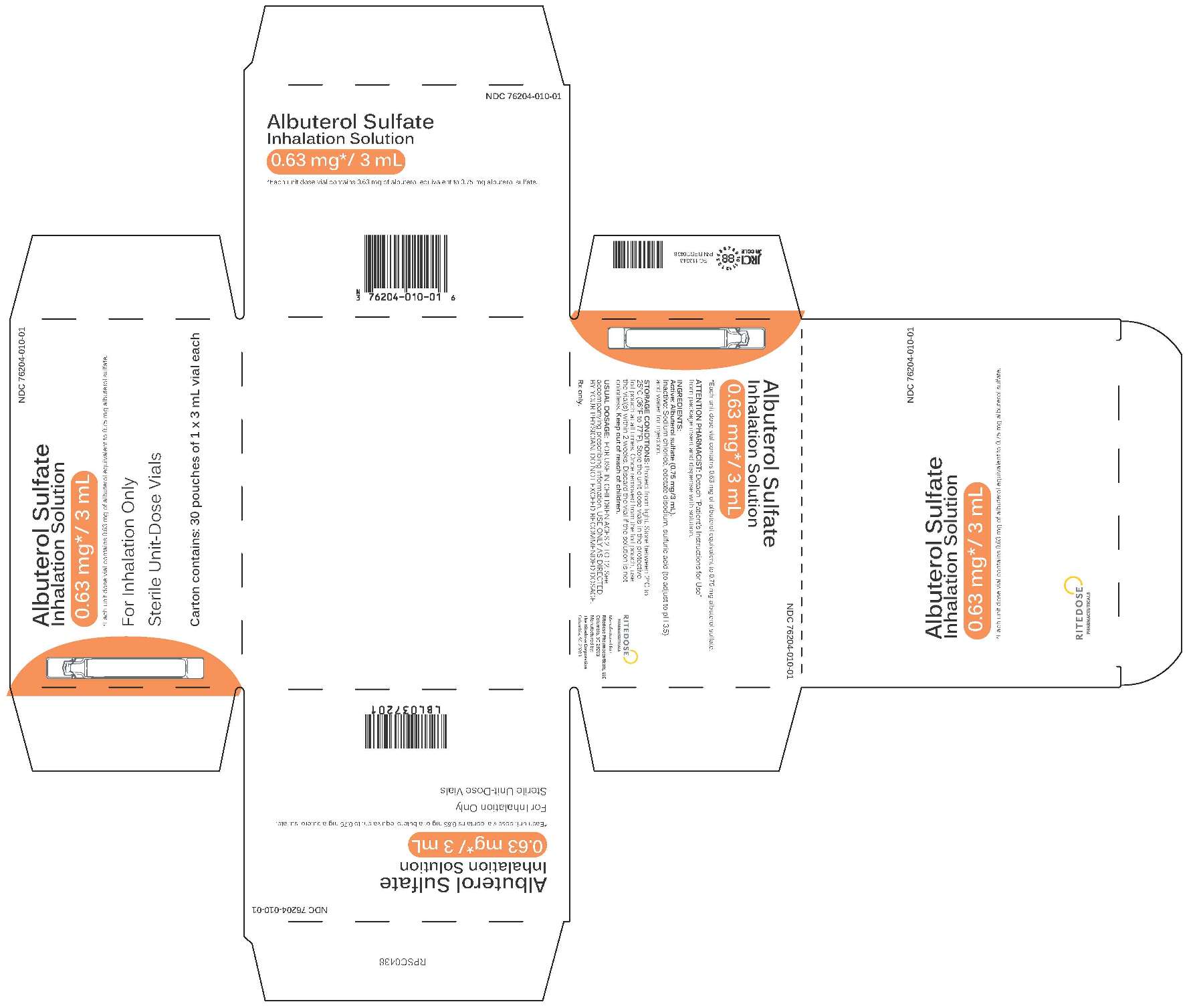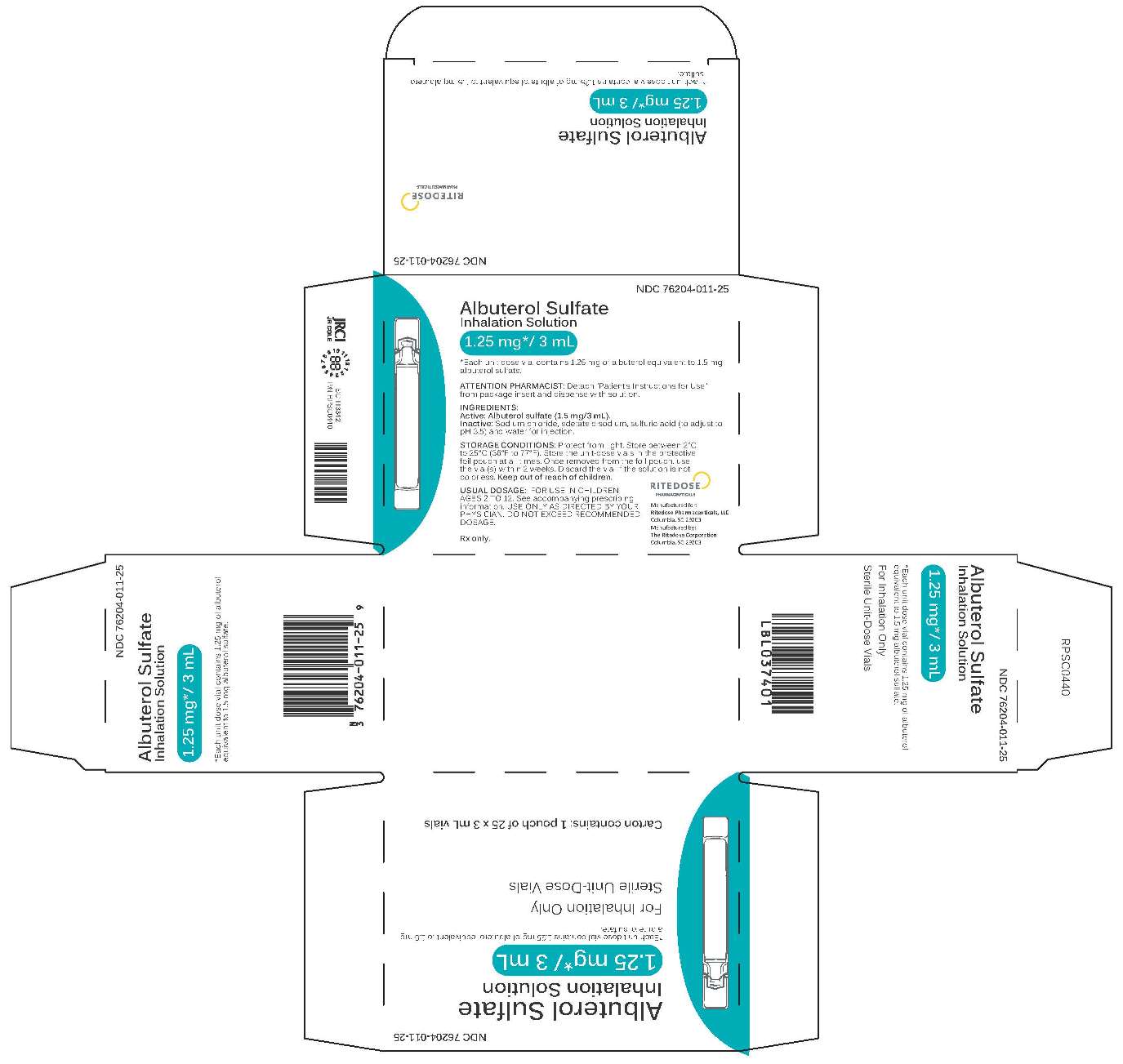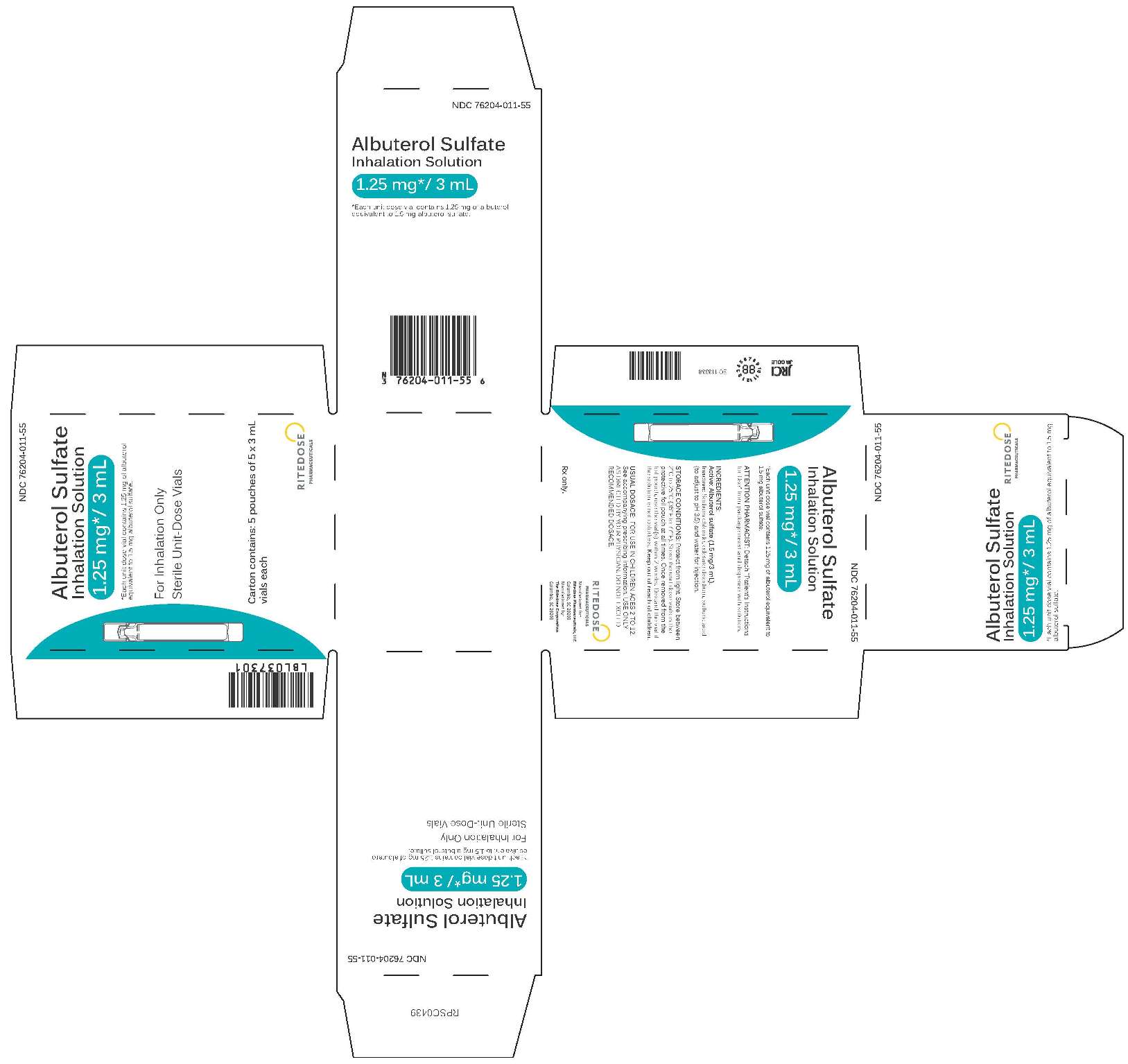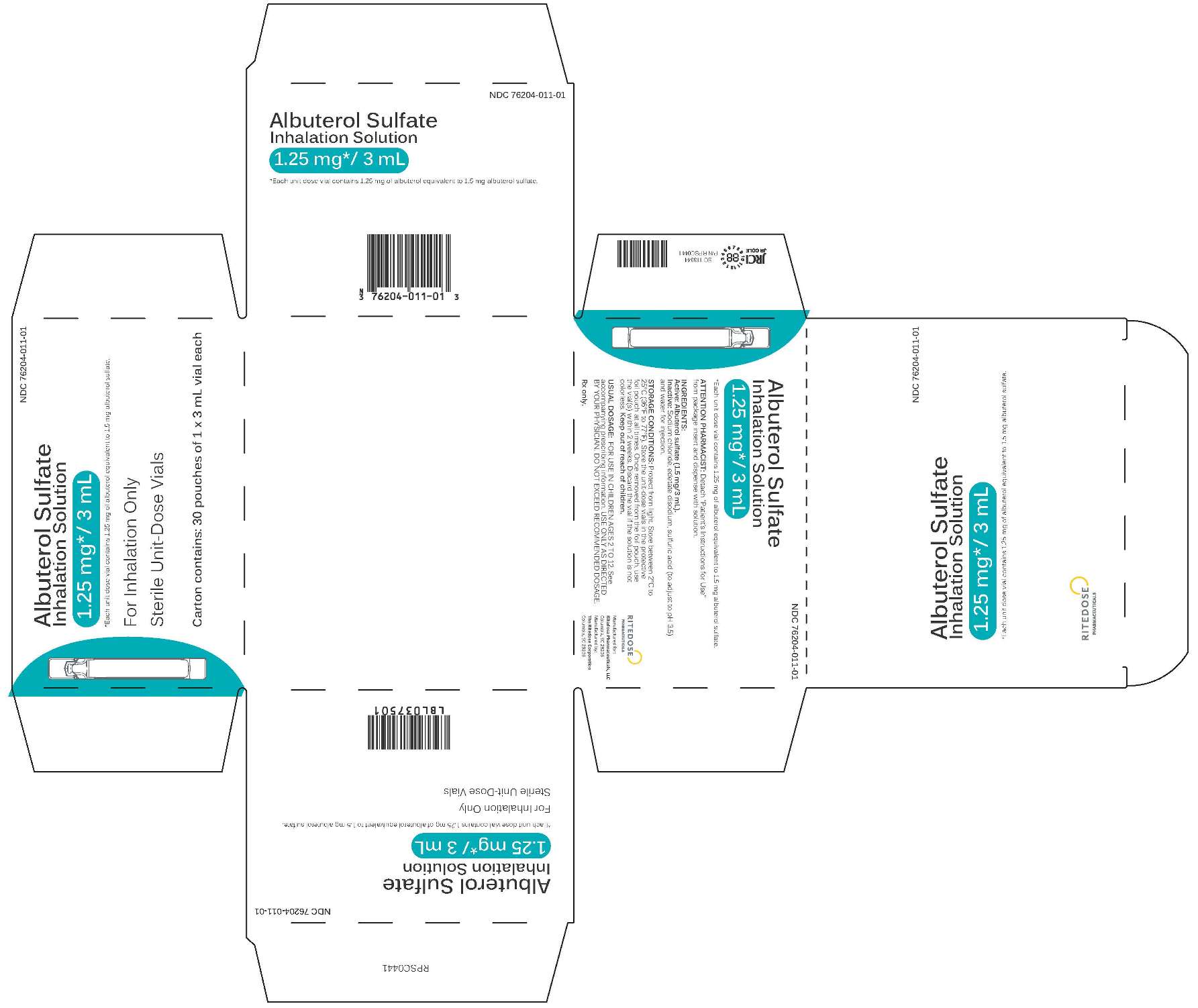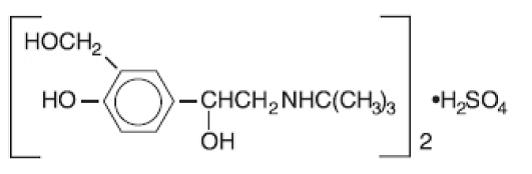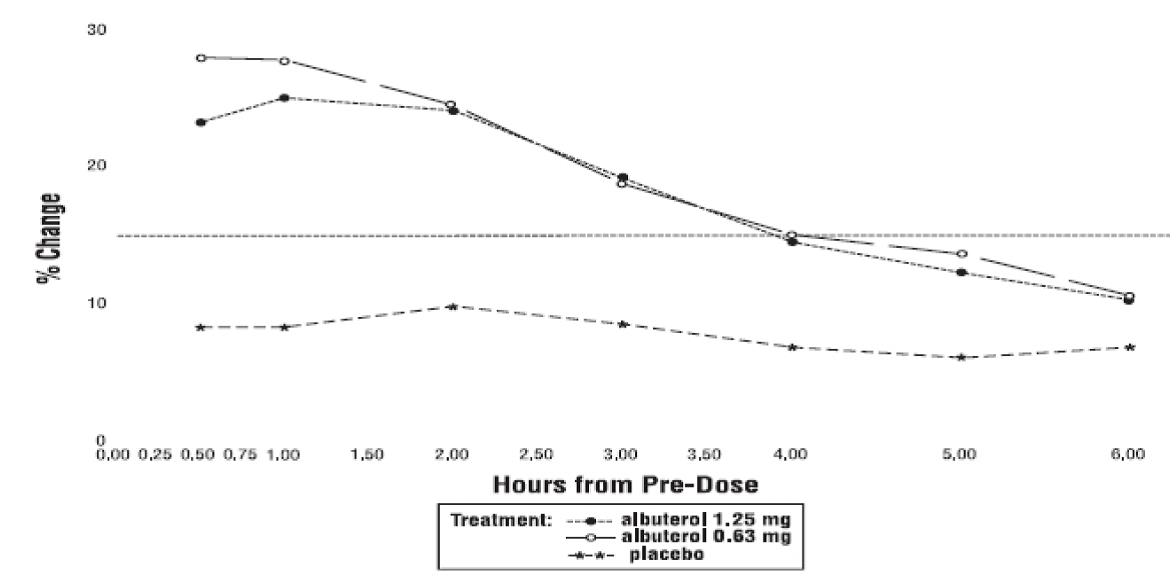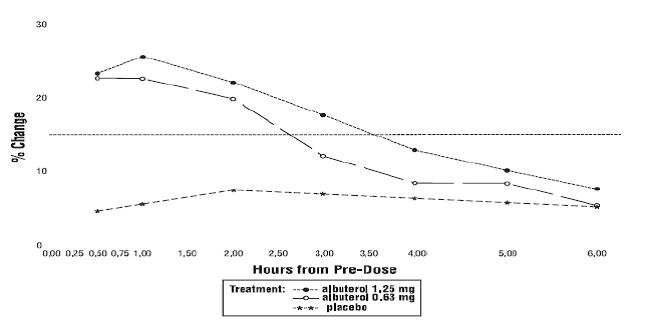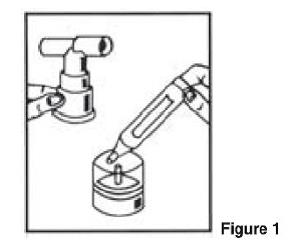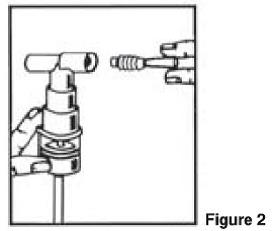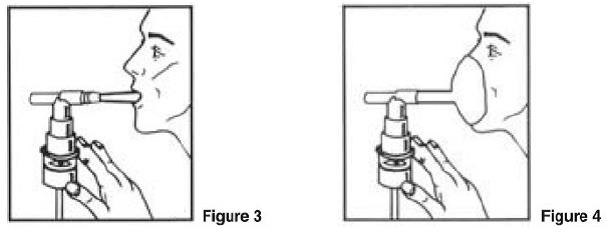 DRUG LABEL: Albuterol Sulfate Inhalation Solution
NDC: 76204-011 | Form: SOLUTION
Manufacturer: Ritedose Pharmaceuticals, LLC
Category: prescription | Type: HUMAN PRESCRIPTION DRUG LABEL
Date: 20251210

ACTIVE INGREDIENTS: ALBUTEROL SULFATE 1.25 mg/3 mL
INACTIVE INGREDIENTS: EDETATE DISODIUM; SODIUM CHLORIDE; SULFURIC ACID

Albuterol Sulfate Inhalation Solution 0.63 mg/3 mL and 1.25 mg/3 mL

DESCRIPTION

Albuterol sulfate inhalation solution is a sterile, clear, colorless solution of the sulfate salt of racemic albuterol, albuterol sulfate. Albuterol sulfate is a relatively selective beta2 - adrenergic bronchodilator (see CLINICAL PHARMACOLOGY). The chemical name for albuterol sulfate is α1 [(tert-butylamino) methyl]-4-hydroxy-m-xylene-α, α’-diol sulfate (2:1) (salt), and its established chemical structure is as follows:

The molecular weight of albuterol sulfate is 576.7 and the empirical formula is (C13 H21NO3)2 • H2SO4. Albuterol sulfate is a white crystalline powder, soluble in water and slightly soluble in ethanol. The World Health Organization recommended name for albuterol is salbutamol.

Albuterol Sulfate Inhalation Solution is supplied in two strengths in unit dose vials. Each unit dose vial contains either 0.63 mg of albuterol equivalent to 0.75 mg of albuterol sulfate or 1.25 mg of albuterol equivalent to 1.5 mg of albuterol sulfate with sodium chloride, edetate disodium (EDTA), and sulfuric acid in a 3-mL isotonic, sterile, aqueous solution. Sodium chloride is added to adjust isotonicity of the solution, EDTA is added as a stabilizer for the active pharmaceutical ingredient, and sulfuric acid is added to adjust pH of the solution to 3.5 (see HOW SUPPLIED).

Albuterol Sulfate Inhalation Solution does not require dilution prior to administration by nebulization. For Albuterol Sulfate Inhalation Solution, like all other nebulized treatments, the amount delivered to the lungs will depend on patient factors, the jet nebulizer utilized, and compressor performance. Using the Pari LC Plus™ nebulizer (with face mask or mouthpiece) connected to a Pari PRONEB™ compressor, under in vitro conditions, the mean delivered dose from the mouth piece (% nominal dose) was approximately 43% of albuterol (1.25 mg strength) and 39% of albuterol (0.63 mg strength) at a mean flow rate of 3.6 L/min. The mean nebulization time was 15 minutes or less. Albuterol Sulfate Inhalation Solution should be administered from a jet nebulizer at an adequate flow rate, via a mouthpiece or face mask (see DOSAGE AND ADMINISTRATION).

CLINICAL PHARMACOLOGY

The prime action of beta-adrenergic drugs is to stimulate adenyl cyclase, the enzyme which catalyzes the formation of cyclic-3’,5’-adenosine monophosphate (cyclic AMP) from adenosine triphosphate (ATP). The cyclic AMP thus formed mediates the cellular responses. In vitro studies and in vivo pharmacologic studies have demonstrated that albuterol has a preferential effect on beta2-adrenergic receptors compared with isoproterenol. While it is recognized that beta2-adrenergic receptors are the predominant receptors in bronchial smooth muscle, recent data indicate that 10% to 50% of the beta-receptors in the human heart may be beta2-receptors. The precise function of these receptors, however, is not yet established. Controlled clinical studies and other clinical experience have shown that inhaled albuterol, like other beta-adrenergic agonist drugs, can produce a significant cardiovascular effect in some patients, as measured by pulse rate, blood pressure, symptoms, and/or electrocardiographic changes. Albuterol is longer acting than isoproterenol in most patients by any route of administration because it is not a substrate for the cellular uptake processes for catecholamines nor for catechol-O-methyl transferase.

Pharmacokinetics

Studies in asthmatic patients have shown that less than 20% of a single albuterol dose was absorbed following either intermittent positive-pressure breathing (IPPB) or nebulizer administration; the remaining amount was recovered from the nebulizer and apparatus, and expired air. Most of the absorbed dose was recovered in urine collected during the 24 hours after drug administration. Following oral administration of 4 mg albuterol, the elimination half-life was five to six hours. Following a 3 mg dose of nebulized albuterol in adults, the mean maximum albuterol plasma level at 0.5 hours was 2.1 ng/mL (range, 1.4 to 3.2 ng/mL). The pharmacokinetics of albuterol following administration of 0.63 mg or 1.25 mg albuterol sulfate inhalation solution by nebulization have not been determined in children 2 to 12 years old.

Animal Pharmacology/Toxicology

Intravenous studies in rats with albuterol sulfate have demonstrated that albuterol crosses the blood-brain barrier and reaches brain concentrations amounting to approximately 5% of plasma concentrations. In structures outside the blood-brain barrier (pineal and pituitary glands), albuterol concentrations were found to be 100 times those found in whole brain.

Studies in laboratory animals (minipigs, rodents, and dogs) have demonstrated the occurrence of cardiac arrhythmias and sudden death (with histologic evidence of myocardial necrosis) when beta-agonists and methylxanthines are administered concurrently. The clinical significance of these findings is unknown.

Clinical Trials

The safety and efficacy of Albuterol Sulfate Inhalation Solution was evaluated in a 4-week, multicenter, randomized, double-blind, placebo-controlled, parallel group study in 349 children 6 to 12 years of age with mild-to-moderate asthma (mean baseline FEV1 60% to 70% of predicted). Approximately half of the patients were also receiving inhaled corticosteroids. Patients were randomized to receive Albuterol Sulfate Inhalation Solution 0.63 mg, Albuterol Sulfate Inhalation Solution 1.25 mg, or placebo three times a day administered via a Pari LC Plus™ nebulizer and a Pari PRONEB™ compressor. Racemic albuterol, delivered by a chlorofluorocarbon (CFC) metered dose inhaler (MDI) or nebulized, was used on an as-needed basis as the rescue medication.

Efficacy, as measured by the mean percent change from baseline in the area under the 6-hour curve for FEV1, was demonstrated for both active treatment regimens (n=112 [1.25 mg group] and n=110 [0.63 mg group]) compared with placebo (n=110) on day 1 and day 28. Figures 1 and 2 illustrate the mean percentage change from pre-dose FEV1 on day 1 and day 28, respectively. The mean baseline FEV1 for all patients was 1.49 L.

Figure1 % Change from Pre-Dose FEV1 Intent-to-Treat Population Day 1

Figure 2 % Change from Pre-Dose FEV1 Intent-to-Treat Population Day 28

The onset of a 15% increase in FEV1 over baseline for both doses of Albuterol Sulfate Inhalation Solution was seen at 30 minutes (the first post-dose assessment). The mean time to peak effect was approximately 30 to 60 minutes for both doses on day 1 and after 4 weeks of treatment. The mean duration of effect, as measured by a >15% increase from baseline in FEV1, was approximately 2.5 hours for both doses on day 1 and approximately 2 hours for both doses after 4 weeks of treatment. In some patients, the duration of effect was as long as 6 hours.

INDICATIONS AND USAGE

Albuterol Sulfate Inhalation Solution is indicated for the relief of bronchospasm in patients 2 to 12 years of age with asthma (reversible obstructive airway disease).

CONTRAINDICATIONS

Albuterol Sulfate Inhalation Solution is contraindicated in patients with a history of hypersensitivity to any of its components.

WARNINGS

Paradoxical Bronchospasm

As with other inhaled beta-adrenergic agonists, Albuterol Sulfate Inhalation Solution can produce paradoxical bronchospasm, which may be life threatening. If paradoxical bronchospasm occurs, Albuterol Sulfate Inhalation Solution should be discontinued immediately and alternative therapy instituted. It should be noted that paradoxical bronchospasm, when associated with inhaled formulations, frequently occurs with the first use of a new canister or vial.

Use of Anti-Inflammatory Agents

The use of beta-adrenergic bronchodilators alone may not be adequate to control asthma in many patients. Early consideration should be given to adding anti-inflammatory agents (e.g., corticosteroids).

Deterioration of Asthma

Asthma may deteriorate acutely over a period of hours or chronically over several days or longer. If the patient needs more doses of Albuterol Sulfate Inhalation Solution than usual, this may be a marker of destabilization of asthma and requires re-evaluation of the patient and the treatment regimen, giving special consideration of the possible need for anti-inflammatory treatment (e.g., corticosteroids).

Fatalities have been reported in association with excessive use of inhaled sympathomimetic drugs and with the home use of nebulizers. It is, therefore, essential that the physician instruct the patient in the need for further evaluation, if his/her asthma becomes worse.

Cardiovascular Effects

Albuterol Sulfate Inhalation Solution, like other beta-adrenergic agonists, can produce a clinically significant cardiovascular effect in some patients as measured by pulse rate, blood pressure, and/or symptoms. Although such effects are uncommon for Albuterol Sulfate Inhalation Solution at recommended doses, if they occur, the drug may need to be discontinued. In addition, beta-agonists have been reported to produce ECG changes, such as flattening of the T-wave, prolongation of the QTc interval, and ST segment depression. The clinical significance of these findings is unknown. Therefore, Albuterol Sulfate Inhalation Solution like all other sympathomimetic amines, should be used with caution in patients with cardiovascular disorders, especially coronary insufficiency, cardiac arrhythmias, and hypertension.

Immediate hypersensitivity reactions may occur after administration of albuterol as demonstrated by rare cases of urticaria, angioedema, rash, bronchospasm, and oropharyngeal edema.

PRECAUTIONS

General

Large doses of intravenous albuterol have been reported to aggravate pre-existing diabetes mellitus and ketoacidosis. As with other beta-agonists, inhaled and intravenous albuterol may produce a significant hypokalemia in some patients, possibly through intracellular shunting, which has the potential to produce adverse cardiovascular effects. The decrease is usually transient, not requiring potassium supplementation.

Information for Patients

The action of Albuterol Sulfate Inhalation Solution may last up to six hours, and therefore it should not be used more frequently than recommended. Do not increase the dose or frequency of medication without consulting your physician. If you find that treatment with Albuterol Sulfate Inhalation Solution becomes less effective for symptomatic relief, your symptoms become worse, and/or you need to use the product more frequently than usual, you should seek medical attention immediately. All asthma medication should only be used under the supervision and direction of a physician. Common effects with medications such as Albuterol Sulfate Inhalation Solution include palpitations, chest pain, rapid heart rate, tremor, or nervousness.

If you are pregnant or nursing, contact your physician about the use of Albuterol Sulfate Inhalation Solution. Effective and safe use of Albuterol Sulfate Inhalation Solution includes an understanding of the way it should be administered.

If the solution in the vial changes color or becomes cloudy, you should not use it.

The drug compatibility (physical and chemical), clinical efficacy, and safety of Albuterol Sulfate Inhalation Solution, when mixed with other drugs in a nebulizer, has not been established.

See illustrated Patient’s Instructions for Use.

Drug Interactions

Other short-acting sympathomimetic aerosol bronchodilators or epinephrine should not be used concomitantly with albuterol sulfate inhalation solution.

Albuterol Sulfate Inhalation Solution should be administered with extreme caution to patients being treated with monoamine oxidase inhibitors or tricyclic antidepressants or within 2 weeks of discontinuation of such agents, since the action of albuterol on the vascular system may be potentiated.

Beta-receptor blocking agents not only block the pulmonary effect of beta-agonists, such as Albuterol Sulfate Inhalation Solution, but may produce severe bronchospasm in asthmatic patients. Therefore, patients with asthma should not normally be treated with beta-blockers. However, under certain circumstances (e.g., prophylaxis after myocardial infarction), there may be no acceptable alternatives to the use of beta-adrenergic blocking agents in patients with asthma. In this setting, cardioselective betablockers should be considered, although they should be administered with caution.

The ECG changes and/or hypokalemia that may result from the administration of non-potassium sparing diuretics (such as loop or thiazide diuretics) can be acutely worsened by beta-agonists, especially when the dose of the beta-agonist is exceeded. Although the clinical significance of these effects is unknown, caution is advised in the co-administration of beta-agonists with non-potassium sparing diuretics.

Mean decreases of 16% to 22% in serum digoxin levels were demonstrated after single dose intravenous and oral administration of albuterol, respectively, to normal volunteers who had received digoxin for 10 days. The clinical significance of these findings for patients with obstructive airway disease who are receiving albuterol and digoxin on a chronic basis is unclear. Nevertheless, it would be prudent to carefully evaluate the serum digoxin levels in patients who are currently receiving digoxin and albuterol.

Carcinogenesis, Mutagenesis, and Impairment of Fertility

In a 2-year study in Sprague-Dawley rats, albuterol sulfate caused a significant dose-related increase in the incidence of benign leiomyomas of the mesovarium and above dietary doses of 2 mg/kg (approximately equivalent to the maximum recommended daily inhalation dose for Albuterol Sulfate Inhalation Solution on a mg/m^2 basis). In another study, this effect was blocked by the co-administration of propranolol, a non-selective beta-adrenergic antagonist.

In an 18-month study in CD-1 mice, albuterol sulfate showed no evidence of tumorigenicity at dietary doses up to 500 mg/kg (approximately 140 times the maximum recommended daily inhalation dose of Albuterol Sulfate Inhalation Solution on a mg/m^2 basis). In a 22-month study in Golden hamsters, albuterol sulfate showed no evidence of tumorigenicity at dietary doses up to 50 mg/kg (approximately 20 times the maximum recommended daily inhalation dose of Albuterol Sulfate Inhalation Solution on a mg/m^2 basis).

Albuterol sulfate was not mutagenic in the Ames test or a mutation test in yeast. Albuterol sulfate was not clastogenic in a human peripheral lymphocyte assay or in an AH1 strain mouse micronucleus assay.

Reproduction studies in rats demonstrated no evidence of impaired fertility at oral doses of albuterol sulfate up to 50 mg/kg (approximately 30 times the maximum recommended daily inhalation dose of Albuterol Sulfate Inhalation Solution on a mg/m^2 basis).

Pregnancy

Teratogenic Effects:

Albuterol has been shown to be teratogenic in mice. A study in CD-1 mice given albuterol subcutaneously showed cleft palate formation in 5 of 111 (4.5%) fetuses at 0.25 mg/kg (less than the maximum recommended daily inhalation dose of Albuterol Sulfate Inhalation Solution on a mg/m^2 basis) and cleft palate formation in 10 of 108 (9.3%) fetuses at 2.5 mg/kg (approximately equal to the maximum recommended daily inhalation dose of Albuterol Sulfate Inhalation Solution on a mg/m^2 basis). The drug did not induce cleft palate formation when administered subcutaneously at a dose of 0.025 mg/kg (less than the maximum recommended daily inhalation dose of Albuterol Sulfate Inhalation Solution on a mg/m^2 basis). Cleft palate formation also occurred in 23 of 72 (30.5%) fetuses from females treated subcutaneously with 2.5 mg/kg isoproterenol (positive control). A reproduction study in Stride rabbits revealed cranioschisis in 7 of 19 (37%) fetuses when albuterol sulfate was administered orally at 50 mg/kg (approximately 60 times the maximum recommended daily inhalation dose of Albuterol Sulfate Inhalation Solution on a mg/m^2 basis).

A study in which pregnant rats were dosed with radiolabelled albuterol sulfate demonstrated that drug related material was transferred from the maternal circulation to the fetus.

There are no adequate and well-controlled studies of the use of albuterol sulfate in pregnant women. Albuterol should be used during pregnancy only if the potential benefit justifies the potential risk to the fetus.

During worldwide marketing experience, various congenital anomalies, including cleft palate and limb defects, have been reported in the offspring of patients being treated with albuterol. Some of the mothers were taking multiple medications during their pregnancies. Because no consistent pattern of defects can be discerned, a relationship between albuterol use and congenital anomalies has not been established.

Labor and Delivery

Oral albuterol has been shown to delay pre-term labor in some reports. There are presently no well-controlled studies that demonstrate that it will stop pre-term labor or prevent labor at term. Because of the potential for beta agonist interference with uterine contractility, use of Albuterol Sulfate Inhalation Solution for relief of bronchospasm during labor should be restricted to those patients in whom the benefits clearly outweigh the risk.

Albuterol has not been approved for the management of pre-term labor. The benefit:risk ratio when albuterol is administered for tocolysis has not been established. Serious adverse reactions, including pulmonary edema, have been reported following administration of albuterol to women in labor.

Nursing Mothers

It is not known whether this drug is excreted in human milk. Because of the potential for tumorigenicity shown for albuterol in some animal studies, a decision should be made whether to discontinue nursing or to discontinue the drug, taking into account the importance of the drug to the mother.

Pediatric Use

Safety and effectiveness of Albuterol Sulfate Inhalation Solution 1.25 mg and 0.63 mg have been established in pediatric patients between the ages of 2 and 12 years. The use of Albuterol Sulfate Inhalation Solution in these age groups is supported by evidence from adequate and well-controlled studies of Albuterol Sulfate Inhalation Solution in children age 6 to 12 years and published reports of albuterol sulfate trials in pediatric patients 3 years of age and older. The safety and effectiveness of Albuterol Sulfate Inhalation Solution in children below 2 years of age have not been established.

ADVERSE REACTIONS

Clinical Trial Experience

Adverse events reported in >1% of patients receiving Albuterol Sulfate Inhalation Solution and more frequently than in patients receiving placebo in a four-week double-blind study are listed in the following table.

Table 1: Adverse Events with an Incidence of >1% of Patients Receiving Albuterol Sulfate Inhalation Solution and Greater than Placebo (expressed as % of treatment group)
 | 1.25 mg Albuterol Sulfate Inhalation Solution (N=115) | 0.63 mg Albuterol Sulfate Inhalation Solution (N=117) | Placebo (N=117)
Asthma Exacerbation | 13 | 11.1 | 8.5
Otitis Media | 4.3 | 0.9 | 0
Allergic Reaction | 0.9 | 3.4 | 1.7
Gastroenteritis | 0.9 | 3.4 | 0.9
Cold Symptoms | 0 | 3.4 | 1.7
Flu Syndrome | 2.6 | 2.6 | 1.7
Lymphadenopathy | 2.6 | 0.9 | 1.7
Skin/Appendage Infection | 1.7 | 0 | 0
Urticaria | 1.7 | 0.9 | 0
Migraine | 0.9 | 1.7 | 0
Chest Pain | 0.9 | 1.7 | 0
Bronchitis | 0.9 | 1.7 | 0.9
Nausea | 1.7 | 0.9 | 0.9

There was one case of ST segment depression in the 1.25 mg Albuterol Sulfate Inhalation Solution treatment group.

No clinically relevant laboratory abnormalities related to Albuterol Sulfate Inhalation Solution administration were seen in this study.

Post-marketing Experience

Metabolic acidosis has been reported after the use of albuterol sulfate inhalation solution. Because this reaction is reported voluntarily from a population of uncertain size, it is not always possible to reliably estimate its frequency or establish a causal relationship to drug exposure.

OVERDOSAGE

The expected symptoms with overdosage are those of excessive beta-adrenergic stimulation and/or occurrence or exaggeration of symptoms such as seizures, angina, hypertension or hypotension, tachycardia with rates up to 200 beats per minute, arrhythmias, nervousness, headache, tremor, dry mouth, palpitation, nausea, dizziness, fatigue, malaise, insomnia, and exaggeration of the pharmacological effects listed in ADVERSE REACTIONS. Hypokalemia may also occur. As with all sympathomimetic aerosol medications, cardiac arrest and even death may be associated with abuse of Albuterol Sulfate Inhalation Solution. Treatment consists of discontinuation of Albuterol Sulfate Inhalation Solution together with appropriate symptomatic therapy. The judicious use of a cardioselective beta-receptor blocker may be considered, bearing in mind that such medication can produce bronchospasm. There is insufficient evidence to determine if dialysis is beneficial for overdosage of Albuterol Sulfate Inhalation Solution.

The oral median lethal dose of albuterol sulfate in mice is greater than 2000 mg/kg (approximately 580 times the maximum recommended daily inhalation dose of Albuterol Sulfate Inhalation Solution on a mg/m^2 basis). The subcutaneous median lethal dose of albuterol sulfate in mature rats and small young rats is approximately 450 mg/kg and 2000 mg/kg, respectively (approximately 260 and 1200 times the maximum recommended daily inhalation dose of Albuterol Sulfate Inhalation Solution on a mg/m^2 basis). The inhalation median lethal dose has not been determined in animals.

DOSAGE AND ADMINISTRATION

The usual starting dosage for patients 2 to 12 years of age is 1.25 mg or 0.63 mg of Albuterol Sulfate Inhalation Solution administered 3 or 4 times daily, as needed, by nebulization. More frequent administration is not recommended.

To administer 1.25 mg or 0.63 mg of albuterol, use the entire contents of one unit-dose vial (3 mL of 1.25 mg or 0.63 mg inhalation solution) by nebulization. Adjust nebulizer flow rate to deliver Albuterol Sulfate Inhalation Solution over 5 to 15 minutes.

The use of Albuterol Sulfate Inhalation Solution can be continued as medically indicated to control recurring bouts of bronchospasm. During this time most patients gain optimum benefit from regular use of the inhalation solution.

Patients 6 to 12 years of age with more severe asthma (baseline FEV1 less than 60% predicted), weight > 40 kg, or patients 11 to 12 years of age may achieve a better initial response with the 1.25 mg dose.

Albuterol Sulfate Inhalation Solution has not been studied in the setting of acute attacks of bronchospasm. A 2.5 mg dose of albuterol provided by a higher concentration product (2.5 mg albuterol per 3 mL) may be more appropriate for treating acute exacerbations, particularly in children 6 years old and above.

If a previously effective dosage regimen fails to provide the usual relief, medical advice should be sought immediately, as this is often a sign of seriously worsening asthma which would require reassessment of therapy.

The drug compatibility (physical and chemical), clinical efficacy and safety of Albuterol Sulfate Inhalation Solution, when mixed with other drugs in a nebulizer have not been established.

The safety and efficacy of Albuterol Sulfate Inhalation Solution have been established in clinical trials when administered using the Pari LC Plus™ nebulizer and Pari PRONEB™ compressor. The safety and efficacy of Albuterol Sulfate Inhalation Solution when administered with other nebulizer systems have not been established.

Albuterol Sulfate Inhalation Solution should be administered via jet nebulizer connected to an air compressor with adequate air flow, equipped with a mouthpiece or suitable face mask.

HOW SUPPLIED

Albuterol Sulfate Inhalation Solution is supplied as a 3 mL, clear, colorless, sterile, preservative-free, aqueous solution in two different strengths, 0.63 mg/3 mL and 1.25 mg/3 mL, of albuterol (equivalent to 0.75 mg of albuterol sulfate or 1.5 mg of albuterol sulfate per 3 mL) in unit-dose low-density polyethylene (LDPE) vials. Each unit-dose LDPE vial is protected in a foil pouch, and each foil pouch contains 1, 5, or 25unit-dose LDPE vials. Each strength of Albuterol Sulfate Inhalation Solution is available in a shelf carton containing a single or multiple foil pouches.

Albuterol Sulfate Inhalation Solution, 0.63 mg/3 mL (potency expressed as albuterol) contains 0.75 mg albuterol sulfate per 3 mL in unit-dose vials and is available in the following packaging configurations.
NDC 76204-010-01 30 foil pouches, each containing 1 vial, total 30 vials per carton
NDC 76204-010-55 5 foil pouches, each containing 5 vials, total 25 vials per carton
NDC 76204-010-25 1 foil pouch, containing 25 vials, total 25 vials per carton

Albuterol Sulfate Inhalation Solution, 1.25 mg/3 mL (potency expressed as albuterol) contains 1.5 mg albuterol sulfate per 3 mL in unit-dose vials and is available in the following packaging configurations.
NDC 76204-011-01 30 foil pouches, each containing 1 vial, total 30 vials per carton
NDC 76204-011-55 5 foil pouches, each containing 5 vials, total 25 vials per carton
NDC 76204-011-25 1 foil pouch, containing 25 vials, total 25 vials per carton

Rx only.

STORAGE

Store between 2°C to 25°C (36°F to 77°F). Protect from light and excessive heat.

Store unit-dose vials in protective foil pouch at all times. Once removed from the foil pouch, use vial(s) within two weeks. Discard the vial if the solution is not colorless.

Keep out of the reach of children.

The brands listed are trademarks of their respective owners.

Manufactured for:
Ritedose Pharmaceuticals, LLC
Columbia, SC 29203 U.S.A.

Manufactured by:
The Ritedose Corporation
Columbia, SC 29203 U.S.A.

RPIN0159 May 2022

PATIENT INFORMATION

Albuterol Sulfate Inhalation Solution

(al bue' ter ol sul' fate)
0.63 mg*/3 mL and 1.25 mg*/3 mL
(*Equivalent to 0.75 mg of albuterol sulfate or 1.5 mg of albuterol sulfate per 3 mL)

Read the patient information that comes with Albuterol Sulfate Inhalation Solution before using it and each time you get a refill for your child. There may be new information. This leaflet does not take the place of talking to your child’s doctor about your child’s medical condition or treatment.

What is Albuterol Sulfate Inhalation Solution?

Albuterol Sulfate Inhalation Solution is a medicine that is used for the relief of bronchospasms caused by asthma in children ages 2 to 12 years. Bronchospasm is the tightening and swelling of the muscles around the airways. Albuterol Sulfate Inhalation Solution can help relax these airway muscles for up to 6 hours so that your child may breathe more easily.

Who should not use Albuterol Sulfate Inhalation Solution?

Do not give your child Albuterol Sulfate Inhalation Solution if he or she is allergic to any of its ingredients. The active ingredient is albuterol sulfate. See the end of this leaflet for a complete list of ingredients.

What should I tell my child’s doctor before giving Albuterol Sulfate Inhalation Solution?

Tell your child’s doctor about all of your child’s medical conditions including if your child has:

- Heart problems
- High blood pressure
- Seizures
- A thyroid problem called hyperthyroidism
- Diabetes

Tell your child’s doctor about all the medicines your child takes, including prescription and nonprescription medicines, vitamins and herbal supplements. Albuterol Sulfate Inhalation Solution and some other medicines can affect each other and may cause serious side effects. Especially tell your child’s doctor if your child is taking or using:

- Any short-acting bronchodilator medicines (sometimes called rescue inhalers)
- Epinephrine
- Medicines called monoamine oxidase inhibitors (MAOIs) or tricycllic anti-depressants or has stopped taking them in the past 2 weeks. These medicines are usually used for mental problems.
- Medicines called beta-blockers (used for heart problems and high blood pressure)
- Certain diuretic medicines (water pills)
- Digoxin

Know the medicines your child takes. Keep a list of them and show it to your child’s doctor and pharmacist each time your child gets a new medicine.

How should Albuterol Sulfate Inhalation Solution be given?

Read the Patient’s Instructions for Use that comes with Albuterol Sulfate Inhalation Solution. Ask your pharmacist for these instructions if they are not with your medicine. Keep the instructions with Albuterol Sulfate Inhalation Solution because you may want to read them again.

Give Albuterol Sulfate Inhalation Solution exactly as prescribed for your child. Do not change your child’s dose or how often it is used without talking to your child’s doctor first.

Albuterol Sulfate Inhalation Solution is breathed into the lungs. Albuterol Sulfate Inhalation Solution is used with a special breathing machine called a nebulizer. Do not mix other medicines with Albuterol Sulfate Inhalation Solution in the nebulizer. Do not use Albuterol Sulfate Inhalation Solution that is not clear and colorless.

- Call your child’s doctor or get emergency help right away if your child’s breathing is not helped or gets worse during treatment with Albuterol Sulfate Inhalation Solution.
- Call your child’s doctor right away if your child needs to use Albuterol Sulfate Inhalation Solution more often than prescribed.
- Albuterol Sulfate Inhalation Solution has not been studied for treating acute attacks of bronchospasm (rescue use). Your child may need a different medicine for rescue use.
- If you give your child too much Albuterol Sulfate Inhalation Solution call your child’s doctor right away.

What are the side effects with Albuterol Sulfate Inhalation Solution?

Albuterol Sulfate Inhalation Solution may cause the following serious side effects:

- Worsening of the tightening and swelling of the muscles around your child’s airways (bronchospasm). This side effect can be life threatening. Call your child’s doctor or get emergency help right away if your child’s breathing is not helped or gets worse during treatment with Albuterol Sulfate Inhalation Solution.
- Serious and life threatening allergic reactions.

Symptoms of a serious allergic reaction include:

- Hives, rash
- Swelling of your child’s face, eyelids, lips, tongue, or throat, and trouble swallowing
- Worsening of your child’s breathing problems such as wheezing, chest tightness or shortness of breath
- Shock (loss of blood pressure and consciousness).

The most common side effects with Albuterol Sulfate Inhalation Solution include a fast or irregular heartbeat, chest pain, shakiness, or nervousness.

How should Albuterol Sulfate Inhalation Solution be stored?

- Store Albuterol Sulfate Inhalation Solution at room temperature, 2° C to 25° C (36° F to 77° F) in its tightly closed container.
- Protect vials from light before use. Therefore, keep unused vials in the foil pouch or carton. Once removed from the foil pouch, use vial(s) within two weeks.
- Do not use Albuterol Sulfate Inhalation Solution after the expiration (EXP) date printed on the vial.
- Do not use Albuterol Sulfate Inhalation Solution that is not clear and colorless.
- Safely, discard Albuterol Sulfate Inhalation Solution that is out-of-date or no longer needed.
- Keep Albuterol Sulfate Inhalation Solution and all medicines out of the reach of children.

General Information about Albuterol Sulfate Inhalation Solution

Medicines are sometimes prescribed for conditions that are not mentioned in the patient information leaflets. Do not use Albuterol Sulfate Inhalation Solution for a condition for which it was not prescribed. Do not give Albuterol Sulfate Inhalation Solution to other people, even if they have the same symptoms your child has. It may harm them.

This leaflet summarizes the most important information about Albuterol Sulfate Inhalation Solution. If you would like more information, talk with your child’s doctor. You can ask your child’s doctor or pharmacist for information about Albuterol Sulfate Inhalation Solution that is written for health professionals.

To report SUSPECTED ADVERSE REACTIONS, contact Ritedose Pharmaceuticals, LLC at 1-855-806-3300 or FDA at 1-800-FDA-1088 or www.fda.gov/medwatch.

What are the ingredients in Albuterol Sulfate Inhalation Solution?

Active Ingredient: albuterol sulfate

Inactive Ingredients : sodium chloride, edetate disodium (EDTA), and sulfuric acid

Rx only

Manufactured for:
Ritedose Pharmaceuticals, LLC
Columbia, SC 29203 U.S.A.

Manufactured by:
The Ritedose Corporation
Columbia, SC 29203 U.S.A.

PATIENT'S INSTRUCTIONS FOR USE

Albuterol Sulfate Inhalation Solution

0.63 mg*/3 mL and 1.25 mg*/3 mL

(*Equivalent to 0.75 mg of albuterol sulfate or 1.5 mg of albuterol sulfate per 3 mL)

Read this patient information completely every time your prescription is filled as information may have changed. Keep these instructions with your medication, as you may want to read them again.

Albuterol Sulfate Inhalation Solution should only be used under the direction of a physician. Your physician and pharmacist have more information about Albuterol Sulfate Inhalation Solution and the condition for which it has been prescribed. Contact them if you have additional questions.

Storing your Medicine

Store Albuterol Sulfate Inhalation Solution between 2°C to 25°C (36°F to 77°F). Vials should be protected from light before use, therefore, keep unused vials in the foil pouch. Do not use after the expiration (EXP) date printed on the vial.

Dose

Albuterol Sulfate Inhalation Solution is supplied as a single-dose, ready-to-use vial containing 3 mL of solution. No mixing or dilution is needed. Use one new vial with each nebulizer treatment.

Instructions for Use

1. Remove one vial from the foil pouch. Place remaining vials back into foil pouch for storage.

2. Twist the cap completely off the vial and squeeze the contents into the nebulizer reservoir (Figure 1).

3. Connect the nebulizer to the mouthpiece or face mask (Figure 2).

4. Connect the nebulizer to the compressor.

5. Sit in a comfortable, upright position; place the mouthpiece in your mouth (Figure 3) or put on the face mask (Figure 4); and turn on the compressor.

6. Breathe as calmly, deeply and evenly as possible through your mouth until no more mist is formed in the nebulizer chamber (about 5-15 minutes). At this point, the treatment is finished.

7. Clean the nebulizer (see manufacturer’s instructions).

Manufactured for:
Ritedose Pharmaceuticals, LLC
Columbia, SC 29203 U.S.A.

Manufactured by:
The Ritedose Corporation
Columbia, SC 29203 U.S.A.

RPIN0159 May 2022